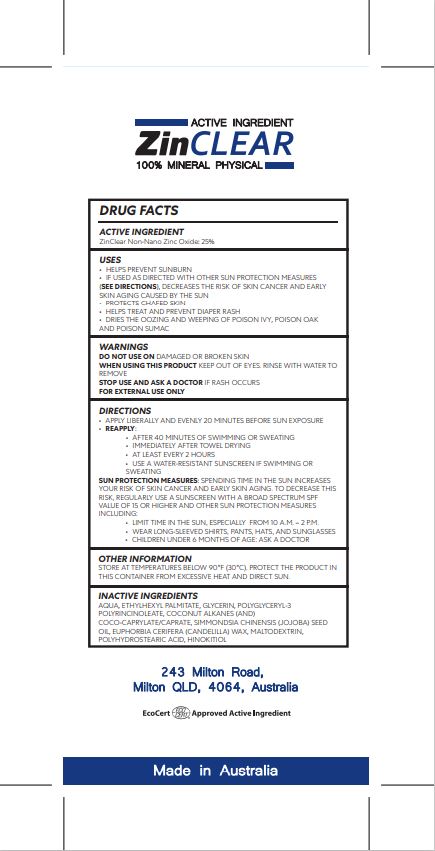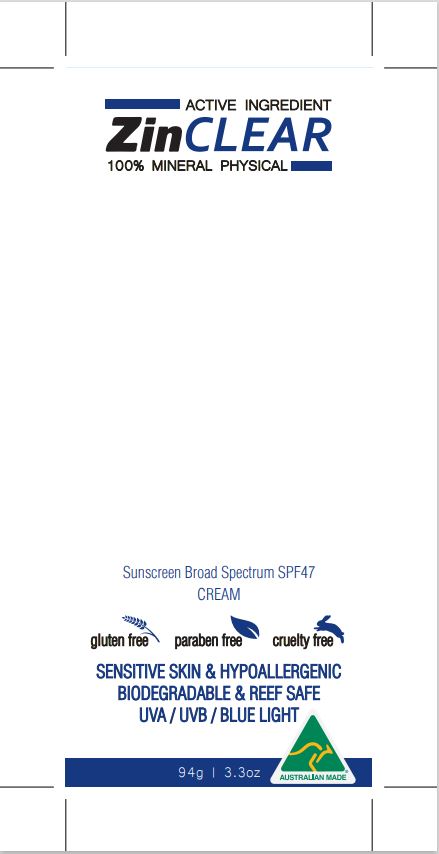 DRUG LABEL: Zinxation SPF 47
NDC: 60396-9999 | Form: LOTION
Manufacturer: Antaria Pty Ltd
Category: otc | Type: HUMAN OTC DRUG LABEL
Date: 20210812

ACTIVE INGREDIENTS: ZINC OXIDE 25 g/100 g
INACTIVE INGREDIENTS: POLYGLYCERYL-3 RICINOLEATE; POLYHYDROXYSTEARIC ACID (2300 MW); MALTODEXTRIN; ISOSTEARIC ACID; POTASSIUM CETYL PHOSPHATE; SODIUM HINOKITIOL; WATER; ETHYLHEXYL PALMITATE; GLYCERIN; COCO-CAPRYLATE/CAPRATE; JOJOBA OIL; SODIUM CHLORIDE; CANDELILLA WAX; ETHYLENEDIAMINE TETRAETHANOL

Recipe 100